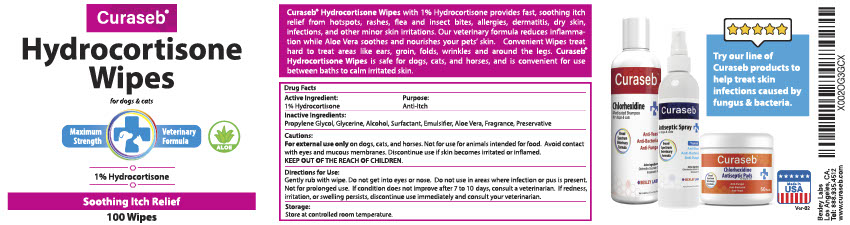 DRUG LABEL: Curaseb
NDC: 86133-001 | Form: CLOTH
Manufacturer: Bexley Labs
Category: animal | Type: OTC ANIMAL DRUG LABEL
Date: 20211228

ACTIVE INGREDIENTS: HYDROCORTISONE ACETATE 1 g/100 g
INACTIVE INGREDIENTS: PROPYLENE GLYCOL; GLYCERIN; ALCOHOL; OCTOXYNOL-9; Triethanolamine Lauryl Sulfate; LAURYL ALCOHOL; ALOE VERA LEAF

Curaseb® Hydrocortisone Wipe

PURPOSE

Curaseb® Hydrocortisone Wipes with 1% Hydrocortisone provides fast, soothing itch relief from hotspots, rashes, flea and insect bites, allergies, dermatitis, dry skin, infections, and other minor skin irritations. Our non-stinging formula reduces inflammation while aloe vera & vitamin E soothes and nourishes your pets' skin. Convenient wipes treat hard to treat areas like ears, groin, folds, wrinkles, and around the legs. Curaseb® Hydrocortisone Wipes is safe for dogs, cats, and horses and is convenient for use between baths to calm irritated skin.

Active: Hydrocortisone 1%

Purpose: Anti-Itch

INACTIVE INGREDIENT

Ethanol, Propylene Glycol, Glycerine, Surfactant, Emulsifier, Aloe Vera, Fragrance, Preservative

WARNINGS AND PRECAUTIONS

For external use only on dogs, cats, and horses. Not for use for animals intended for food. Avoid contact with eyes and mucous membranes. Discontinue use if skin becomes irritated or inflamed.

KEEP OUT OF THE REACH OF CHILDREN.

INSTRUCTIONS FOR USE

Gently rub with wipe. Do not get into eyes or nose. Do not use in areas where infection or pus is present. Not for prolonged use. If conditions do not improve after 7 TO 10 days, consult a veterinarian. If redness, irritation, or swelling persists, discontinue use immediately and consult your veterinarian.

STORAGE AND HANDLING

Store at controlled room temperature.

Made in USA

Manufactured for: Bexley Labs Los Angeles, CA

Tel: 888.935.4512

www.curaseb.com

X002OG3GCX

VER-02

PACKAGE LABEL

Curaseb®

Hydrocortisone Wipes for dogs & cats

Maximum Strength Veterinary Formula

1% Hydrocortisone

Soothing Itch Relief

100 Wipes